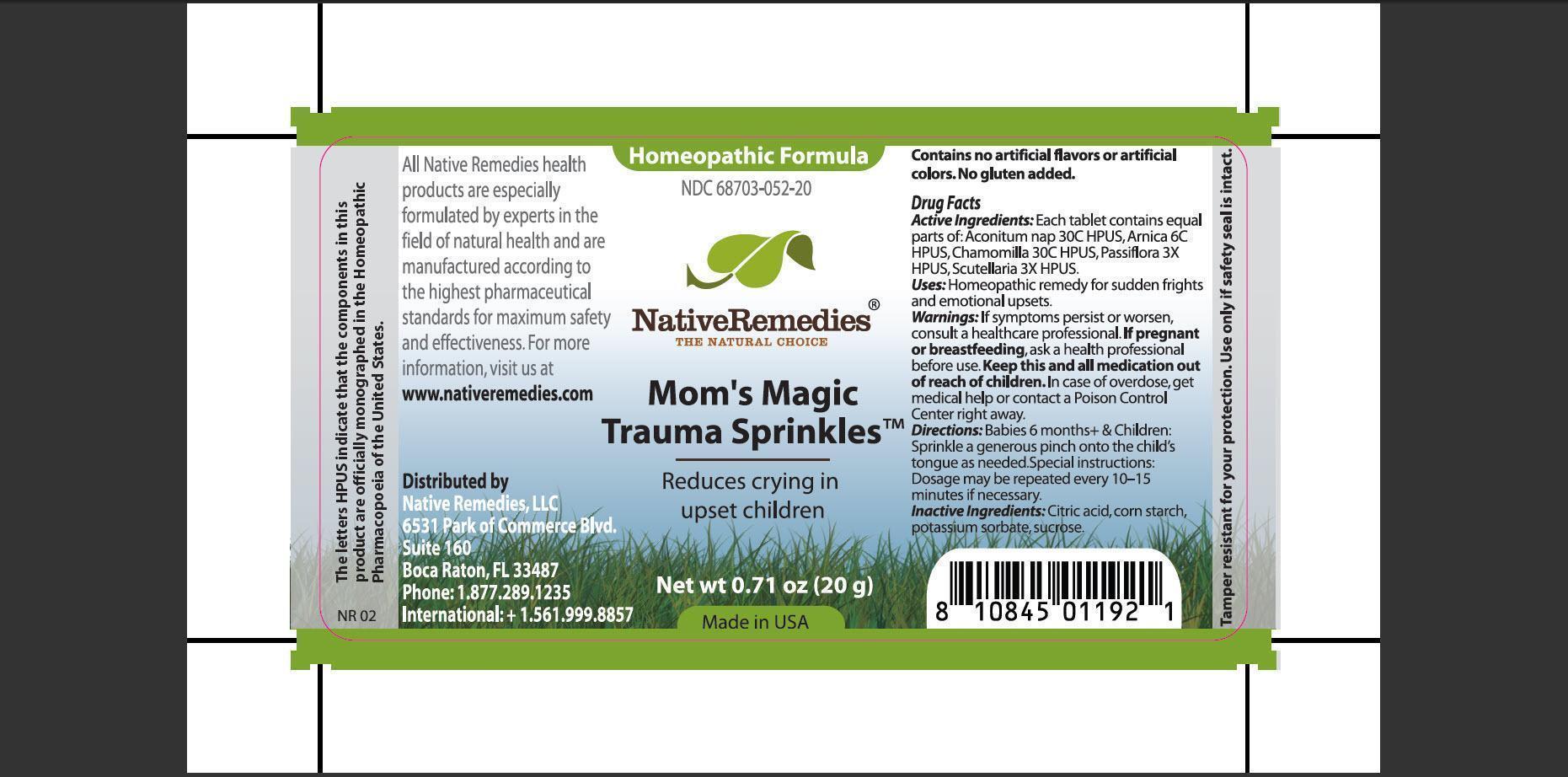 DRUG LABEL: Moms Magic Trauma Sprinkles
NDC: 68703-052 | Form: GRANULE
Manufacturer: Native Remedies, LLC
Category: homeopathic | Type: HUMAN OTC DRUG LABEL
Date: 20130117

ACTIVE INGREDIENTS: ACONITUM NAPELLUS 30 [hp_C]/16 mg; ARNICA MONTANA 6 [hp_C]/16 mg; MATRICARIA RECUTITA 30 [hp_C]/16 mg; PASSIFLORA INCARNATA FLOWERING TOP 3 [hp_X]/16 mg; SCUTELLARIA LATERIFLORA 3 [hp_X]/16 mg
INACTIVE INGREDIENTS: CITRIC ACID MONOHYDRATE; STARCH, CORN; POTASSIUM SORBATE; SUCROSE

Mom's Magic Trauma Sprinkles

PURPOSE

Reduces crying in upset children

ACTIVE INGREDIENT

Active Ingredients: Each tablet contains equal parts of: Aconitum nap 30C HPUS, Arnica 6C HPUS, Chamomilla 30C HPUS, Passiflora 3X HPUS, Scutellaria 3X HPUS.

INDICATIONS AND USAGE

Uses: Homeopathic remedy for sudden frights and emotional upsets.

WARNINGS

Warnings: If symptoms persist or worsen, consult a healthcare professional.

PREGNANCY OR BREAST FEEDING

If pregnant or breastfeeding, ask a health professional before use.

KEEP OUT OF REACH OF CHILDREN

Keep this and all medication out of reach of children.

OVERDOSAGE

In case of overdose, get medical help or contact a Poison Control Center right away.

DOSAGE AND ADMINISTRATION

Directions: Babies 6 month+ and Children: Sprinkle a generous pinch onto the child's tongue as needed. Special instructions: Dosage may be repeated every 10-15 minutes if necessary.

INACTIVE INGREDIENT

Inactive Ingredients:Citric acid, corn starch, potassium sorbate, sucrose.

PATIENT COUNSELING INFORMATION

The letters HPUS indicate that the components in this product are officially monographed in the Homeopathic Pharmacopoeia of the United States.

All Native Remedies health products are especially formulated by experts in the field of natural health and are manufactures according to the highest pharmaceutical standards for maximum safety and effectiveness. For more information, visit us at www.nativeremedies.com

Distributed by
Native Remedies, LLC
6531 Park of Commerce Blvd.
Suite 160
Boca Raton, Fl 33487
Phone: 1.877.289.1235
International: +1.561.999.8857

Contains no artificial flavors or artificial colors. No gluten added.

STORAGE AND HANDLING

Tamper resistant for your protection. Use only if safety seal is intact.